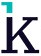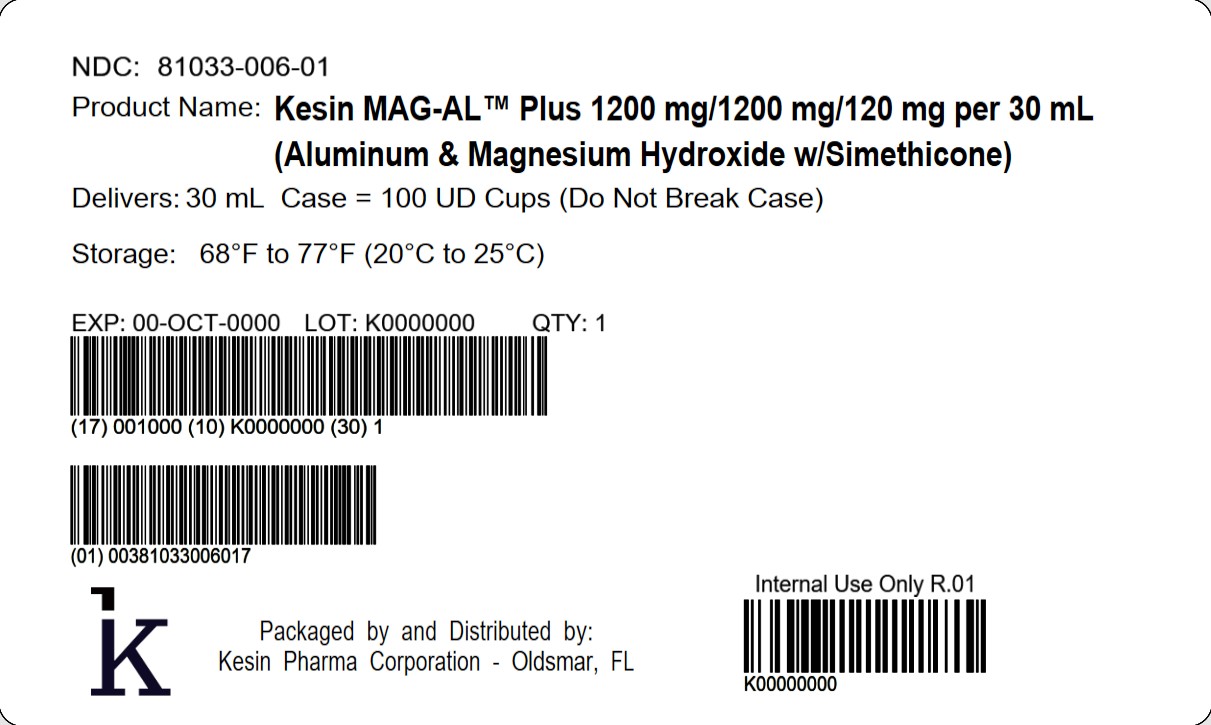 DRUG LABEL: Kesin MAG-AL Plus
NDC: 81033-006 | Form: SUSPENSION
Manufacturer: Kesin Pharma Corporation
Category: otc | Type: HUMAN OTC DRUG LABEL
Date: 20251112

ACTIVE INGREDIENTS: ALUMINUM HYDROXIDE 200 mg/5 mL; MAGNESIUM HYDROXIDE 200 mg/5 mL; DIMETHICONE, UNSPECIFIED 20 mg/5 mL
INACTIVE INGREDIENTS: SUCRALOSE; SILICON DIOXIDE; PROPYLPARABEN; GLYCERIN; PROPYLENE GLYCOL; SORBITOL; MICROCRYSTALLINE CELLULOSE; METHYLPARABEN; MINT; WATER; XANTHAN GUM

Kesin MAG-AL™ Plus (Aluminum & Magnesium Hydroxide w/Simethicone) Suspension

Drug Facts

ACTIVE INGREDIENT

Active ingredient (in each 5 mL = 1 teaspoonful)………………….………..................................Purpose

Aluminum Hydroxide 200 mg……………………………………………………………………………..Antacid

Magnesium Hydroxide 200 mg…………………………………………………………………………...Antacid

Simethicone 20 mg………………………………………………………………………………..............Antigas

Uses

For the relief of:

- acid indigestion
- heartburn
- sour stomach
- upset stomach due to these symptoms
- pressure and bloating commonly referred to as gas

Warnings

Do not take more than 16 teaspoonfuls in a 24-hour period or use the maximum dosage for more than 2 weeks except under the advice and supervision of a physician.

Ask a doctor before use if you have

- kidney disease
- a magnesium-restricted diet

Ask a doctor or pharmacist before use if you are

- presently taking a prescription drug. Antacids may interact with certain prescription drugs.

Stop use and ask a doctor if

- symptoms last more than 2 weeks

PREGNANCY OR BREAST FEEDING

If pregnant or breast-feeding,ask a health professional before use.

Keep out of reach of children.In case of overdose, get medical help or contact a Poison Control Center right away.

Directions

- shake well before using
- do not take more than 16 teaspoonfuls in 24 hours or use the maximum dosage for more than 2 weeks

Age | Dose
adults and children 12 years of age and older | take 2 to 4 teaspoonfuls four times a day or as directed by a physician
children under 12 years of age | consult a physician

Other information

- each teaspoonful (5 mL) contains:magnesium 200 mg, sodium < 1mg
- store at 20°C to 25°C (68°F to 77°F)
- Avoid freezing
- Kesin MAG-AL Plus is a milky-white mint flavored suspension supplied in the following oral dosage forms:

NDC 81033-006-30: 30 mL unit-dose cup
NDC 81033-006-01: Case containing 100 unit-dose cups of 30 mL each.

Inactive ingredients

colloidal silicon dioxide, glycerin, methylparaben, microcrystalline cellulose, mint flavor, propylene glycol, propylparaben, purified water, sorbitol, sucralose, xanthan gum

Questions or comments?

Call 1-833-537-4679

Distributed by:

Kesin Pharma

Oldsmar, FL 34677

PIS-006-V01

Rev. 10/2025

PRINCIPAL DISPLAY PANEL - 30 mL Dose Cup Tray Label

NDC: 81033-006-01

Kesin MAG-AL TM 1200 mg/1200 mg/120 mg per 30 mL

(Aluminum & Magnesium Hydroxide w/Simethicone)

Delivers: 30 mL

Case = 100 UD Cups (Do Not Break Case)